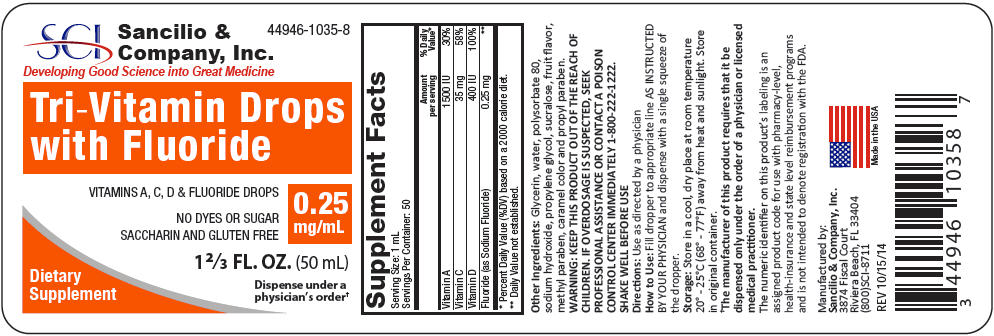 DRUG LABEL: Tri-Vitamin with Fluoride
NDC: 44946-1035 | Form: SOLUTION/ DROPS
Manufacturer: Sancilio & Company Inc
Category: other | Type: DIETARY SUPPLEMENT
Date: 20180306

ACTIVE INGREDIENTS: Vitamin A 1500 [iU]/1 mL; Ascorbic Acid 35 mg/1 mL; Vitamin D 400 [iU]/1 mL; Sodium Fluoride 0.25 mg/1 mL
INACTIVE INGREDIENTS: Glycerin; Water; Polysorbate 80; Sodium hydroxide; Propylene glycol; Sucralose; Methylparaben; Propylparaben

Tri-Vitamin Drops with Fluoride

Ingredients

Vitamin A | 1500 IU
Vitamin C | 35 mg
Vitamin D | 400 IU
Fluoride [Each 1 mL of Tri-Vitamin Drops contains 0.25 mg Fluoride from 0.55 mg Sodium Fluoride (NaF).] (as Sodium Fluoride) | 0.25 mg

Other Ingredients:

Glycerin, water, polysorbate 80, sodium hydroxide, propylene glycol, sucralose, fruit flavor, methyl paraben, caramel color, propyl paraben.

Storage

Store in a cool, dry place at room temperature 20°-25°C (68°-77°F) away from heat and sunlight. Store in original container.

KEEP THIS AND ALL MEDICATIONS OUT OF THE REACH OF CHILDREN. IF OVERDOSAGE IS SUSPECTED, SEEK PROFESSIONAL ASSISTANCE OR CONTACT A POISON CONTROL CENTER IMMEDIATELY 1-800-222-1222.

Caution

Do not use this product if you are allergic to any of the ingredients. Take this product at least 2 hours before or after taking any products containing calcium (including milk, yogurt, other dairy products) or aluminum/magnesium hydroxide (e.g., certain antacids/laxatives) since these may decrease effectiveness.

Prolonged daily ingestion of excessive fluoride may result in varying degrees of dental fluorosis.

This medical food product is formulated to be administered orally, under the supervision of a physician and is intended for the dietary management of dental caries for which a distinctive nutritional requirement of fluoride, based on recognized scientific principles, has been established by medical evaluation. This product is a medical food and is not intended to be used as a drug or dietary supplement.

The numeric identifier on this product's labeling is an assigned product code for use with pharmacy-level, health-insurance and state level reimbursement programs and is not intended to denote registration with the FDA.

SHAKE WELL BEFORE USING

DIRECTIONS

Use as directed by a physician.

How to Use

Fill dropper to appropriate line and dispense with a single squeeze of the dropper bulb. The full dose will be given. It is normal for a small amount to remain in the tip of the dropper.

Do not accept if tamper evident box seal is broken or missing.

HEALTH CLAIM

Manufactured by: Sancilio & Co., Inc. Riviera Beach, FL 33404 USA

PRINCIPAL DISPLAY PANEL - 50 mL Bottle Label

44946-1035-8

SCI
Sancilio &
Company, Inc.
Developing Good Science into Great Medicine

Tri-Vitamin Drops
with Fluoride

VITAMINS A, C, D & FLUORIDE DROPS

NO DYES OR SUGAR
SACCHARIN AND GLUTEN FREE

0.25
mg/mL

1⅔ FL. OZ. (50 mL)

Dispense under a
physician's order†

Dietary
Supplement